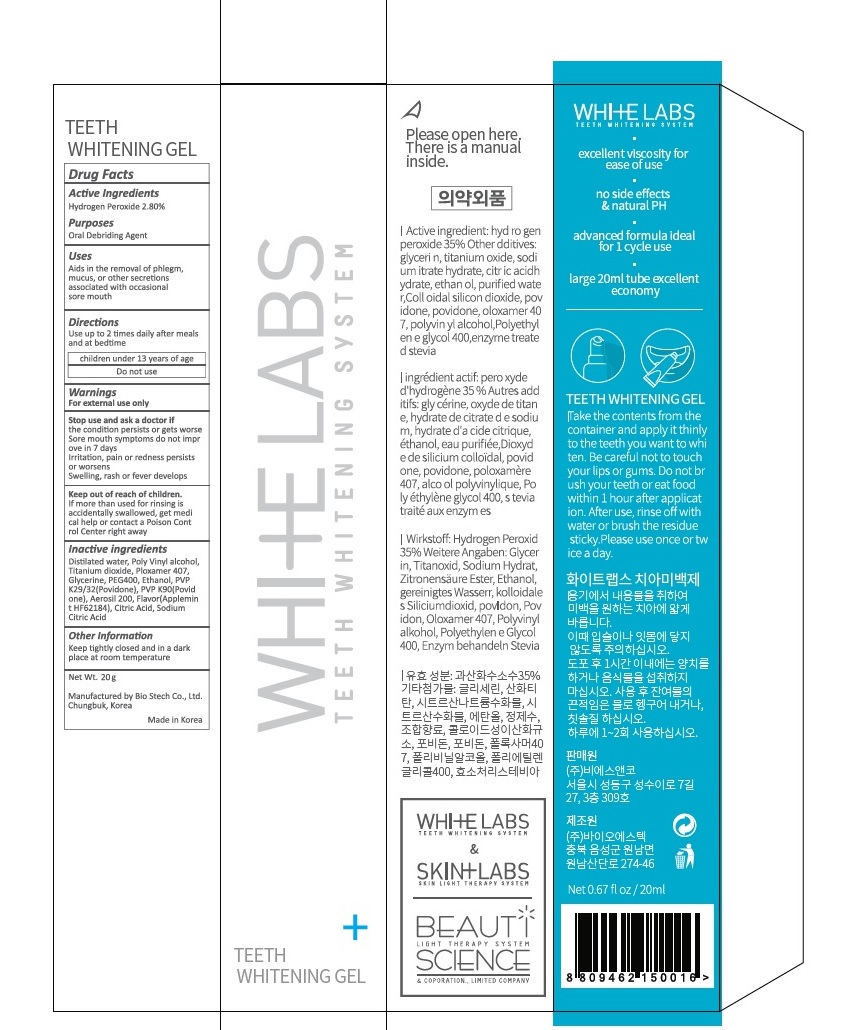 DRUG LABEL: White Labs
NDC: 73660-001 | Form: LIQUID
Manufacturer: BS and Co. Ltd
Category: otc | Type: HUMAN OTC DRUG LABEL
Date: 20200227

ACTIVE INGREDIENTS: HYDROGEN PEROXIDE 2.8 g/100 g
INACTIVE INGREDIENTS: WATER; POLYVINYL ALCOHOL, UNSPECIFIED; TITANIUM DIOXIDE; POLOXAMER 407; GLYCERIN; POLYETHYLENE GLYCOL 400; ALCOHOL; POVIDONE K29/32; POVIDONE K90; SILICON DIOXIDE; MENTHA SUAVEOLENS WHOLE; CITRIC ACID MONOHYDRATE; SODIUM CITRATE, UNSPECIFIED FORM

73660-001

ACTIVE INGREDIENT

Hydrogen Peroxide 2.80%

PURPOSE

Oral Debriding

INDICATIONS AND USAGE

Aids in the removal of phlegm, mucus, or other secretions associated with occasional sore mouth

DOSAGE AND ADMINISTRATION

Use up to 2 times daily after meals and at bedtime

children under 13 years of age Do not use

WARNINGS

For external use only

ASK DOCTOR

The condition persists or gets worse

Sore mouth symptoms do not improve in 7 days

Irritation, pain or redness persists or worsens

Swelling, rash or fever develops

Keep out of reach of children. If more than used for rinsing is accidentally swallowed, get medical help or contact a Poison Control Center right away

INACTIVE INGREDIENT

Distilated water, Polyvinyl alcohol, Titanium dioxide, Poloxamer 407, Glycerine, PEG400, Ethanol, PVP K29/32(Povidone), PVP K90(Povidone), Aerosil 200, Flavor(Applemint HF62184), Citric Acid, Sodium Citric Acid